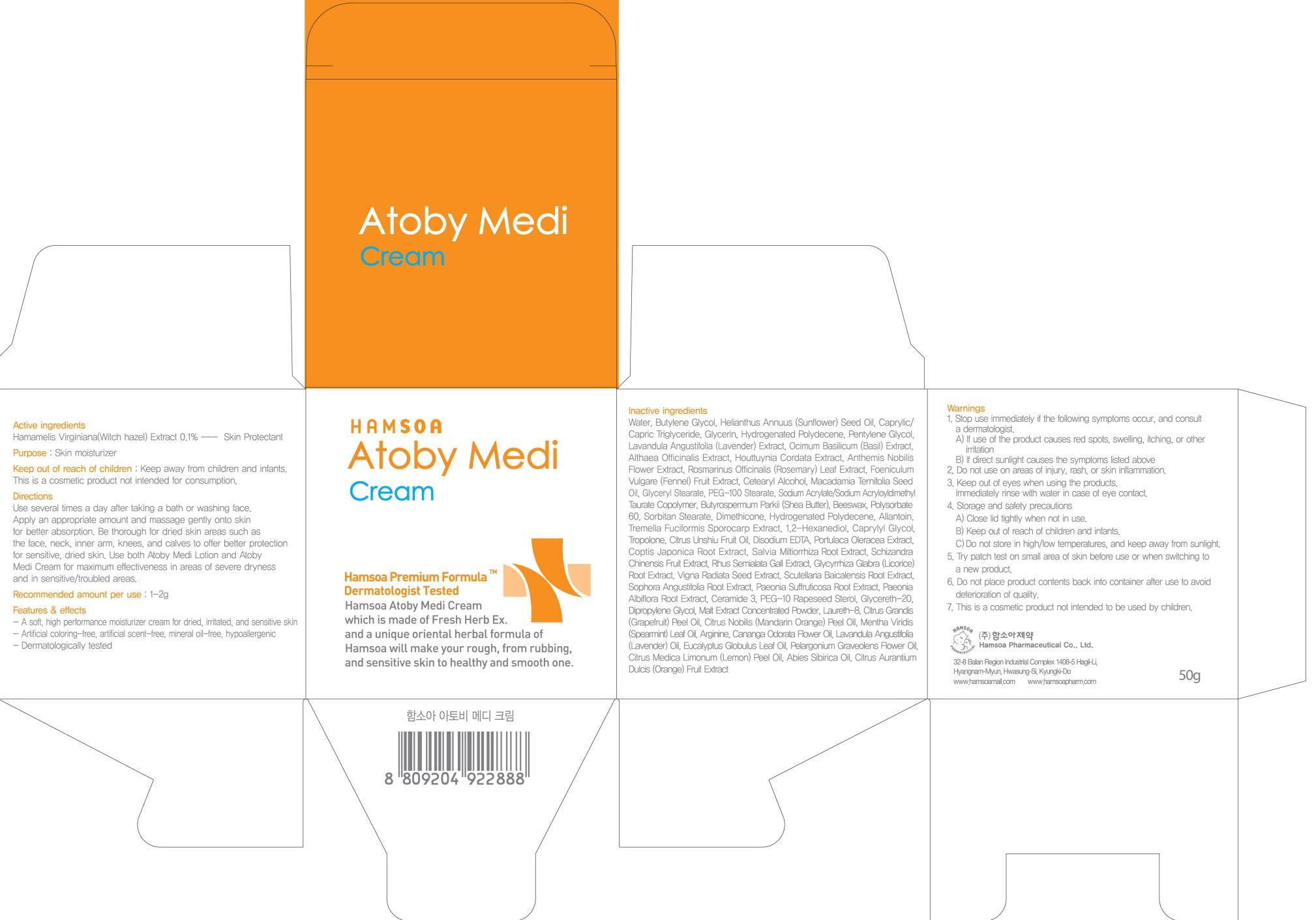 DRUG LABEL: HAMSOA ATOBY MEDI
NDC: 50964-050 | Form: CREAM
Manufacturer: HAMSOA PHARMACEUTICAL CO., LTD.
Category: otc | Type: HUMAN OTC DRUG LABEL
Date: 20120820

ACTIVE INGREDIENTS: WITCH HAZEL 0.05 g/50 g
INACTIVE INGREDIENTS: WATER; BUTYLENE GLYCOL; SUNFLOWER OIL; MEDIUM-CHAIN TRIGLYCERIDES; GLYCERIN; PENTYLENE GLYCOL

Active ingredient

Active ingredient: Witch hazel(Hamamelis Virginiana) 0.1%

Inactive ingredient

Water, Butylene Glycol, Helianthus Annuus (Sunflower) Seed Oil, Caprylic/Capric Triglyceride, Glycerin, Hydrogenated Polydecene, Pentylene Glycol, Lavandula Angustifolia (Lavender) Extract, Ocimum Basilicum (Basil) Extract, Althaea Officinalis Extract, Houttuynia Cordata Extract, Anthemis Nobilis Flower Extract, Rosmarinus Officinalis (Rosemary) Leaf Extract, Foeniculum Vulgare (Fennel) Fruit Extract, Cetearyl Alcohol, Macadamia Ternifolia Seed Oil, Glyceryl Stearate, PEG-100 Stearate, Sodium Acrylate/Sodium Acryloyldimethyl Taurate Copolymer, Butyrospermum Parkii (Shea Butter), Beeswax, Polysorbate 60, Sorbitan Stearate, Dimethicone, Hydrogenated Polydecene, Allantoin, Tremella Fuciformis Sporocarp Extract, 1,2-Hexanediol, Caprylyl Glycol, Tropolone, Citrus Unshiu Fruit Oil, Disodium EDTA, Portulaca Oleracea Extract, Coptis Japonica Root Extract, Salvia Miltiorrhiza Root Extract, Schizandra Chinensis Fruit Extract, Rhus Semialata Gall Extract, Glycyrrhiza Glabra (Licorice) Root Extract, Vigna Radiata Seed Extract, Scutellaria Baicalensis Root Extract, Sophora Angustifolia Root Extract, Paeonia Suffruticosa Root Extract, Paeonia Albiflora Root Extract, Ceramide 3, PEG-10 Rapeseed Sterol, Glycereth-20, Dipropylene Glycol, Malt Extract Concentrated Powder, Laureth-8, Citrus Grandis (Grapefruit) Peel Oil, Citrus Nobilis (Mandarin Orange) Peel Oil, Mentha Viridis (Spearmint) Leaf Oil, Arginine, Cananga Odorata Flower Oil, Lavandula Angustifolia (Lavender) Oil, Eucalyptus Globulus Leaf Oil, Pelargonium Graveolens Flower Oil, Citrus Medica Limonum (Lemon) Peel Oil, Abies Sibirica Oil, Citrus Aurantium Dulcis (Orange) Fruit Extract

Purpose

Purpose: Skin moisturizer

Warnings

1. Stop use immediately if the following symptoms occur, and consult a dermatologist.
A) If use of the product causes red spots, swelling, itching, or other irritation
B) If direct sunlight causes the symptoms listed above
2. Do not use on areas of injury, rash, or skin inflammation.
3. Keep out of eyes when using the products. Immediately rinse with water in case of eye contact.
4. Storage and safety precautions
A) Close lid tightly when not in use.
B) Keep out of reach of children and infants.
C)Do not store in high/low temperatures, and keep away from sunlight.
5. Try patch test on small area of skin before use or when switching to a new product.
6. Do not place product contents back into container after use to avoid deterioration of quality.
7. This is a cosmetic product not intended to be used by children.

KEEP OUT OF REACH OF CHILDREN

Keep away from children and infants.
This is a cosmetic product not intended for consumption.

DOSAGE AND ADMINISTRATION

Recommended amount per use: 1-2g

INDICATIONS AND USAGE

Use several times a day after taking a bath or washing face.
Apply an appropriate amount and massage gently onto skin for better absorption.
Be thorough for dried skin areas such as the face, neck, inner arm, knees, and calves to offer better protection for sensitive, dried skin.
Use both Atoby Medi Lotion and Atoby Medi Cream for maximum effectiveness in areas of severe dryness and in sensitive/troubled areas.